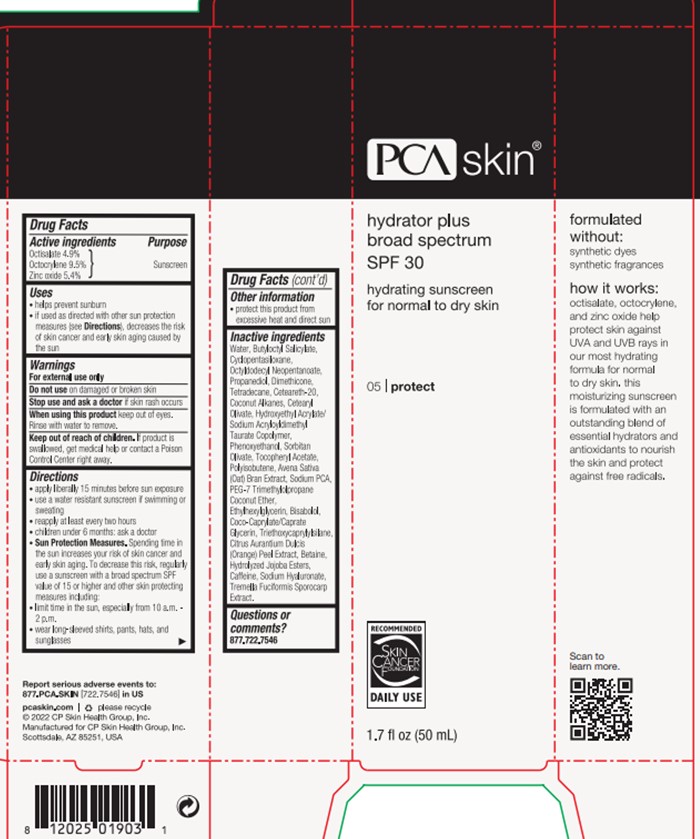 DRUG LABEL: Hydrator Plus
NDC: 68726-263 | Form: LOTION
Manufacturer: CP Skin Health Group, Inc.
Category: otc | Type: HUMAN OTC DRUG LABEL
Date: 20240214

ACTIVE INGREDIENTS: OCTOCRYLENE 10 g/100 mL; OCTISALATE 5 g/100 mL; ZINC OXIDE 5.4 g/100 mL
INACTIVE INGREDIENTS: ORANGE PEEL; HYDROLYZED JOJOBA ESTERS (ACID FORM); HYALURONATE SODIUM; POLYOXYL 20 CETOSTEARYL ETHER; LEVOMENOL; BUTYLOCTYL SALICYLATE; .ALPHA.-TOCOPHEROL ACETATE; POTASSIUM SORBATE; OAT BRAN; SORBITAN OLIVATE; COCONUT ALKANES; TRIETHOXYCAPRYLYLSILANE; CYCLOMETHICONE 5; POLYISOBUTYLENE (1000 MW); CAFFEINE; TETRADECANE; OCTYLDODECYL NEOPENTANOATE; DIMETHICONE; COCOYL CAPRYLOCAPRATE; HYDROXYETHYL ACRYLATE/SODIUM ACRYLOYLDIMETHYL TAURATE COPOLYMER (100000 MPA.S AT 1.5%); SODIUM PYRROLIDONE CARBOXYLATE; TREMELLA FUCIFORMIS FRUITING BODY; PHENOXYETHANOL; PROPANEDIOL; ETHYLHEXYLGLYCERIN; CETEARYL OLIVATE; WATER; GLYCERIN; BETAINE

PCA Skincare Hydrator Plus SPF 30

Active Ingredients

Octisalate (4.9%)

Octocrylene (9.5%)

Zinc Oxide (5.4%)

Purpose

Sunscreen

Uses

Helps prevent sunburn.

If used as directed with other sun protection measures (see Directions), decreases the risk of skin cancer and early skin aging caused by the sun

Warnings

For external use only.

Do not use on damaged or broken skin

Stop use and ask a doctor if skin rash occurs

When using this product keep out of eyes. Rinse with water to remove.

Keep out of reach of children. If product is swallowed, get medical help or contact a Poison Control Center right away.

Directions

Apply liberally 15 minutes before sun exposure

Use a water resistant sunscreen if swimming or sweating

Reapply at least every two hours

Children under 6 months: as a doctor.

Sun Protection Measures. Spending time in the sun increases your risk of skin cancer and early skin aging. To decrease this risk, regularly use a sunscreen with a broad spectrum SPF value of 15 or higher and other skin protecting measures including: limit time in the sun, especially from 10 a.m. - 2 p.m., wear long-sleeved shirts, pants, hats, and sunglasses.

Other Information

Protect this product from excessive heat and direct sun

Inactive Ingredients

Avena Sativa (Oat) Bran Extract

Betaine

Bisabolol

Butyloctyl Salicylate

Caffeine

Ceteareth-20

Cetearyl Olivate

Citrus Aurantium Dulcis (Orange) Peel Extract

Coco-Caprylate/Caprate

Coconut Alkanes

Cyclopentasiloxane

Dimethicone

Ethylhexylgylcerin

Glycerin

Hydrolyzed Jojoba Esters

Hydroxyethyl Acrylate/Sodium Acryloyldimethyl Taurate Copolymer

Octyldodecyl Neopentanoate

PEG-7 Trimethylolpropane Coconut Ether

Phenoxyethanol

Polyisobutene

Propanediol

Sodium Hyaluronate

Sodium PCA

Sorbitan Olivate

Tetradecane

Tocopheryl Acetate

Tremella Fuciformis Sporocarp Extract

Triethoxycaprylylsilane

Water

Questions

Please call 877-722-7546